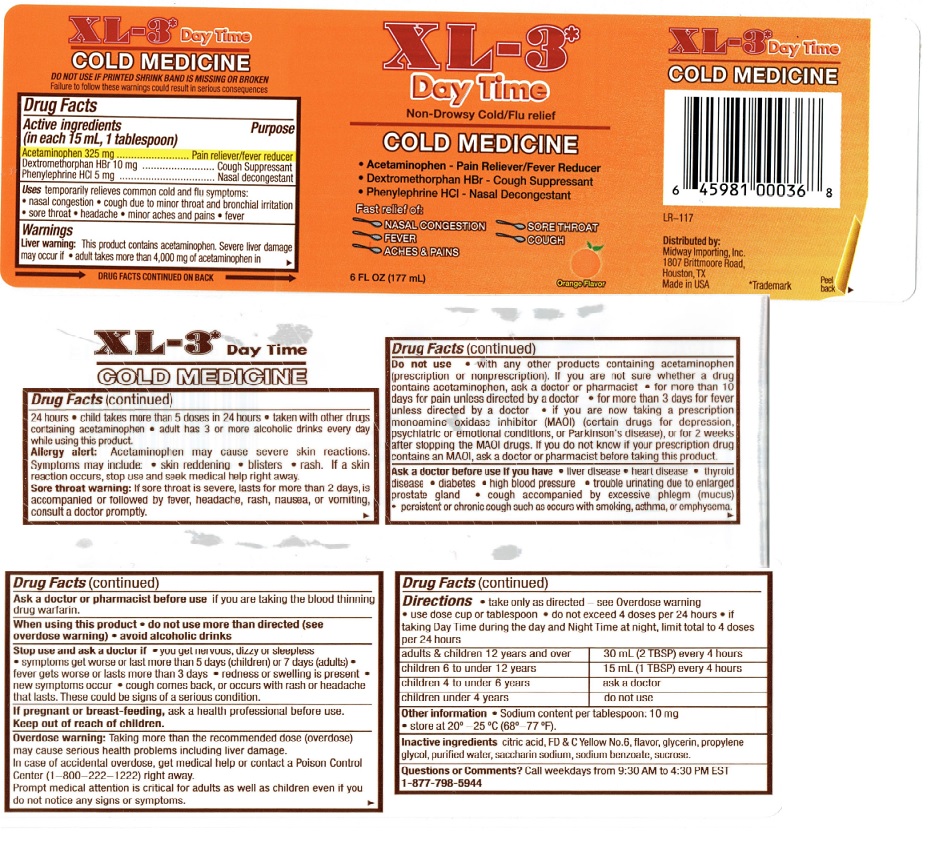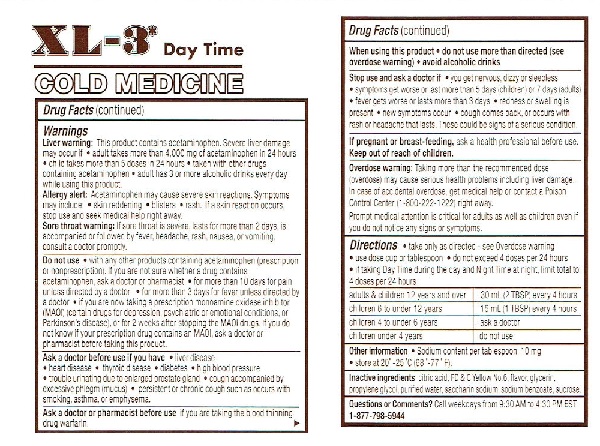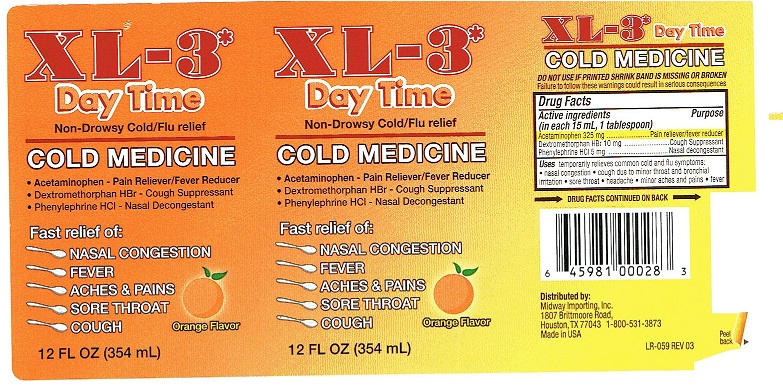 DRUG LABEL: XL-3  Day Time
NDC: 76281-304 | Form: LIQUID
Manufacturer: AptaPharma Inc.
Category: otc | Type: HUMAN OTC DRUG LABEL
Date: 20231230

ACTIVE INGREDIENTS: ACETAMINOPHEN 325 mg/15 mL; DEXTROMETHORPHAN HYDROBROMIDE 10 mg/15 mL; PHENYLEPHRINE HYDROCHLORIDE 5 mg/15 mL
INACTIVE INGREDIENTS: CITRIC ACID MONOHYDRATE; FD&C YELLOW NO. 6; GLYCERIN; PROPYLENE GLYCOL; WATER; SACCHARIN SODIUM; SODIUM BEHENATE; SUCROSE

XL-3* Day Time

Drug Facts

Active ingredients (in each 15 mL, 1 tablespoon)

Acetaminophen 325 mg
Dextromethorphan HBr 10 mg
Phenylephrine HCI 5 mg

Purpose

Pain reliever/fever reducer
Cough Suppressant
Nasal decongestant

Uses

temporarily relieves common cold and flu symptoms:
• nasal congestion • cough due to minor throat and bronchial
irritation • sore throat • headache • minor aches and pains • fever

Warnings

Liver warning: This product contains acetaminophen. Severe liver damage may occur if • adult takes more than 4,000 mg of acetaminophen in 24 hours • child takes more than 5 doses in 24 hours • taken with other drugs containing acetaminophen • adult has 3 or more alcoholic drinks every day while using this product.

Allergy alert: Acetaminophen may cause severe skin reactions. Symptoms
may include: • skin reddening • blisters • rash. If a skin reaction occurs,
stop use and seek medical help right away.

Sore throat warning: If sore throat is severe, lasts for more than 2 days, is
accompanied or followed by fever, headache, rash, nausea, or vomiting,
consult a doctor promptly.

Do not use

• with any other products containing acetaminophen (prescription or nonprescription). lf you are not sure whether a drug contains acetaminophen, ask a doctor or pharmacist • for more than10 days for pain unless directed by a doctor • for more than 3 days for fever unless directed by a doctor • if you are now taking a prescription monoamine oxidase inhibitor (MAOI) (certain drugs for depression, psychiatric or emotional conditions, or Parkinson’s disease), or for 2 weeks after stopping the MAOI drugs. If you do not know if your prescription drug contains an MAOI, ask a doctor or pharmacist before taking this product.

Ask a doctor before use if you have

• liver disease
• heart disease • thyroid disease • diabetes • high blood pressure
• trouble urinating due to enlarged prostate gland • cough accompanied by
excessive phlegm (mucus) • persistent or chronic cough such as occurs with smoking, asthma, or emphysema.

Ask a doctor or pharmacist before use

if you are taking the blood thinning drug warfarin

When using this product

• do not use more than directed (see
overdose warning) • avoid alcoholic drinks

Stop use and ask a doctor if

• you get nervous, dizzy or sleepless
• symptoms get worse or last more than 5 days (children) or 7days (adults)
• fever gets worse or lasts more than 3 days • redness or swelling is
present • new symptoms occur • cough comes back, or occurs with
rash or headache that lasts. These could be signs of a serious condition.

PREGNANCY OR BREAST FEEDING

If pregnant or breast-feeding, ask a health professional before use.

Keep out of reach of children.

Overdose warning:

Taking more than the recommended dose
(overdose) may cause serious health problems including liver damage.
In case of accidental overdose, get medical help or contact a Poison
Control Center (1-800-222-1222) right away.
Prompt medical attention is critical for adults as well as children even if
you do not notice any signs or symptoms.

DOSAGE AND ADMINISTRATION

Directions • take only as directed - see Overdose warning
• use dose cup or tablespoon • do not exceed 4 doses per 24 hours
• if taking Day Time during the day and Night Time at night, limit total to
4 doses per 24 hours
adults & children 12 years and over 30 mL (2 TBSP) every 4 hours
children 6 to under 12 years 15mL (1TBSP) every 4 hours
children 4 to under 6 years ask a doctor
children under 4 years do not use

Other information

• Sodium content per tablespoon: 10mg
• store at 20°-25°C (68°-77° F).

Inactive ingredients

citric acid, FD & C Yellow No.6, flavor, glycerin,
propylene glycol, purified water, saccharin sodium, sodium benzoate, sucrose.

Questions or Comments?

Call weekdays from 9:30 AM to 4:30 PM EST
1-877-798-5944

Principal Display Package

XL-3*
Day Time
Non-Drowsy Cold/Flu relief

COLD MEDICINE

• Acetaminophen - Pain Reliever/Fever Reducer
• Dextromethorphan HBr - Cough Suppressant
• Phenylephrine HCI - Nasal Decongestant

Fast Relief of:
NASAL CONGESTION
FEVER
ACHES & PAINS
SORE THROAT
COUGH

12 FL OZ (354 mL) Orange Flavor

XL-3*
Day Time
Non-Drowsy Cold/Flu relief

COLD MEDICINE

• Acetaminophen - Pain Reliever/Fever Reducer
• Dextromethorphan HBr - Cough Suppressant
• Phenylephrine HCI - Nasal Decongestant

Fast Relief of:
NASAL CONGESTION
FEVER
ACHES & PAINS
SORE THROAT
COUGH

12 FL OZ (354 mL) Orange Flavor

XL-3* Day Time

COLD MEDICINE

DO NOT USE IF PRINTED SHRINK BAND IS MISSING OR BROKEN
Failure to follow these warnings could result in serious consequences

Drug Facts
Active ingredients Purpose
(in each 15 mL, 1 tablespoon)
Acetaminophen 325 mg ........................ Pain reliever/fever reducer
Dextromethorphan HBr 10 mg .........................Cough Suppressant
Phenylephrine HCI 5 mg .................................Nasal decongestant

Uses temporarily relieves common cold and flu symptoms:
• nasal congestion • cough due to minor throat and bronchial
irritation • sore throat • headache • minor aches and pains • fever

→ DRUG FACTS CONTINUED ON BACK →

Distributed by:
Midway Importing, Inc.
1807 Brittmoore Road,
Houston, TX 77043 1-800-531-3873
Made in USA
Peel
LR-059 REV 03 back ►

XL-3* Day Time

COLD MEDICINE

Drug Facts (continued)

Warnings
Liver warning: This product contains acetaminophen. Severe liver damage may occur if • adult takes more than 4,000 mg of acetaminophen in 24 hours • child takes more than 5 doses in 24 hours • taken with other drugs containing acetaminophen • adult has 3 or more alcoholic drinks every day while using this product.
Allergy alert: Acetaminophen may cause severe skin reactions. Symptoms
may include: • skin reddening • blisters • rash. If a skin reaction occurs,
stop use and seek medical help right away.
Sore throat warning: If sore throat is severe, lasts for more than 2 days, is
accompanied or followed by fever, headache, rash, nausea, or vomiting,
consult a doctor promptly.

Do not use • with any other products containing acetaminophen (prescription or nonprescription). lf you are not sure whether a drug contains acetaminophen, ask a doctor or pharmacist • for more than10 days for pain unless directed by a doctor • for more than 3 days for fever unless directed by a doctor • if you are now taking a prescription monoamine oxidase inhibitor (MAOI) (certain drugs for depression, psychiatric or emotional conditions, or Parkinson’s disease), or for 2 weeks after stopping the MAOI drugs. If you do not know if your prescription drug contains an MAOI, ask a doctor or pharmacist before taking this product.

Ask a doctor before use if you have • liver disease
• heart disease • thyroid disease • diabetes • high blood pressure
• trouble urinating due to enlarged prostate gland • cough accompanied by
excessive phlegm (mucus) • persistent or chronic cough such as occurs with smoking, asthma, or emphysema.

Ask a doctor or pharmacist before use if you are taking the blood thinning drug warfarin. ►

Drug Facts (continued)

When using this product • do not use more than directed (see
overdose warning) • avoid alcoholic drinks

Stop use and ask a doctor if • you get nervous, dizzy or sleepless
• symptoms get worse or last more than 5 days (children) or 7days (adults)
• fever gets worse or lasts more than 3 days • redness or swelling is
present • new symptoms occur • cough comes back, or occurs with
rash or headache that lasts. These could be signs of a serious condition.

If pregnant or breast-feeding, ask a health professional before use.
Keep out of reach of children.

Overdose warning: Taking more than the recommended dose
(overdose) may cause serious health problems including liver damage.
In case of accidental overdose, get medical help or contact a Poison
Control Center (1-800-222-1222) right away.
Prompt medical attention is critical for adults as well as children even if
you do not notice any signs or symptoms.

Directions • take only as directed - see Overdose warning
• use dose cup or tablespoon • do not exceed 4 doses per 24 hours
• if taking Day Time during the day and Night Time at night, limit total to
4 doses per 24 hours
___________________________________________________________
adults & children 12 years and over │ 30 mL (2 TBSP) every 4 hours
___________________________________________________________
children 6 to under 12 years │ 15mL (1TBSP) every 4 hours
___________________________________________________________
children 4 to under 6 years │ ask a doctor
___________________________________________________________
children under 4 years │ do not use
___________________________________________________________
Other information • Sodium content per tablespoon: 10mg
• store at 20°-25°C (68°-77° F).

Inactive ingredients citric acid, FD & C Yellow No.6, flavor, glycerin,
propylene glycol, purified water, saccharin sodium, sodium benzoate, sucrose.

Questions or Comments? Call weekdays from 9:30 AM to 4:30 PM EST
1-877-798-5944

XL-3*
Day Time
Non-Drowsy Cold/Flu relief

COLD MEDICINE

• Acetaminophen - Pain Reliever/Fever Reducer
• Dextromethorphan HBr - Cough Suppressant
• Phenylephrine HCI - Nasal Decongestant

Fast Relief of:
NASAL CONGESTION
FEVER
ACHES & PAINS
SORE THROAT
COUGH

6 FL OZ (177 mL) Orange Flavor